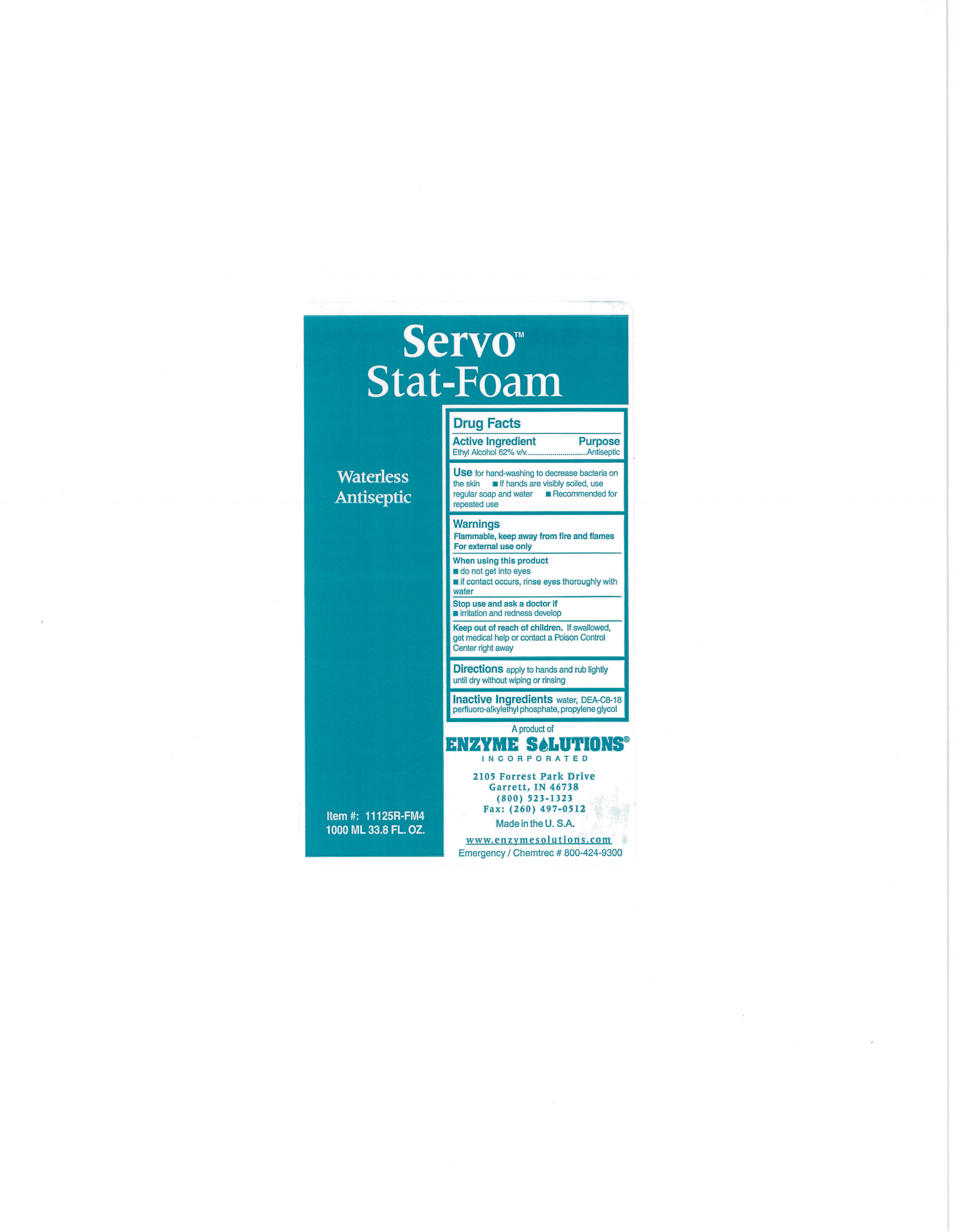 DRUG LABEL: Servo Stat-Foam
NDC: 76378-011 | Form: LIQUID
Manufacturer: Enzyme Solutions, Inc.
Category: otc | Type: HUMAN OTC DRUG LABEL
Date: 20241126

ACTIVE INGREDIENTS: ALCOHOL 62 mL/100 mL
INACTIVE INGREDIENTS: WATER; DIETHANOLAMINE BIS(C8-C18 PERFLUOROALKYLETHYL)PHOSPHATE; PROPYLENE GLYCOL

Drug Facts 76378-011

Active Ingredient

Ethyl Alcohol 62% v/v

Purpose

Antiseptic

Use

for hand-washing to decrease bacteria on the skin

If hands are visibly soiled, use regular soap and water

Recommended for repeated use

Warnings

Flammable, keep away from fire and flames

For external use only

When using this product

do not get into eyes

if contact occurs, rinse eyes thoroughly with water

Stop use and ask a doctor if

irritation and redness develop

Keep out of reach of children.

If swallowed, get medical help or contact a Poison Control Center right away

Directions

apply to hands and rub lightly until dry without wiping or rinsing

Inactive Ingredients

water, DEA-C8-18 perfluoro-alkylethyl phosphate, propylene glycol

PACKAGE LABEL

Servo

Stat-Foam

Waterless

Antiseptic

Item #: 11125R-FM4

1000ML 33.8 FL. OZ.